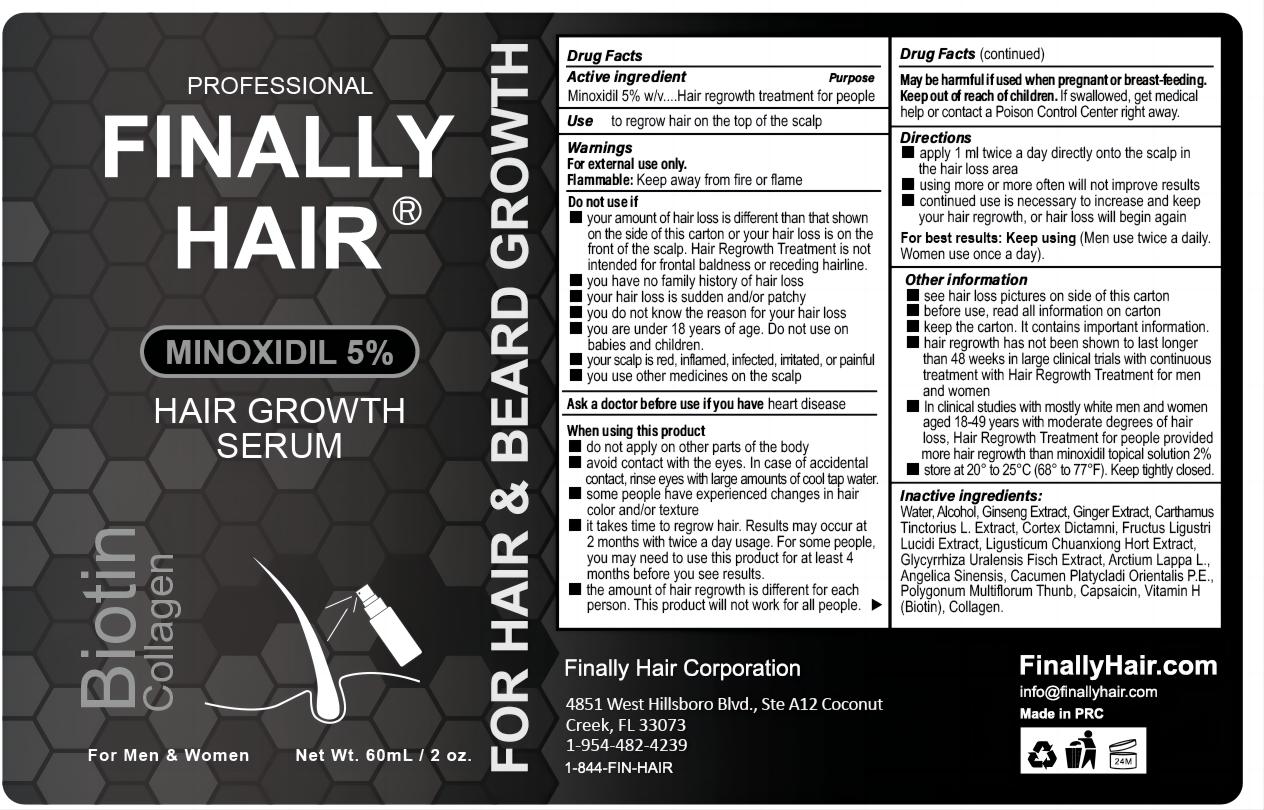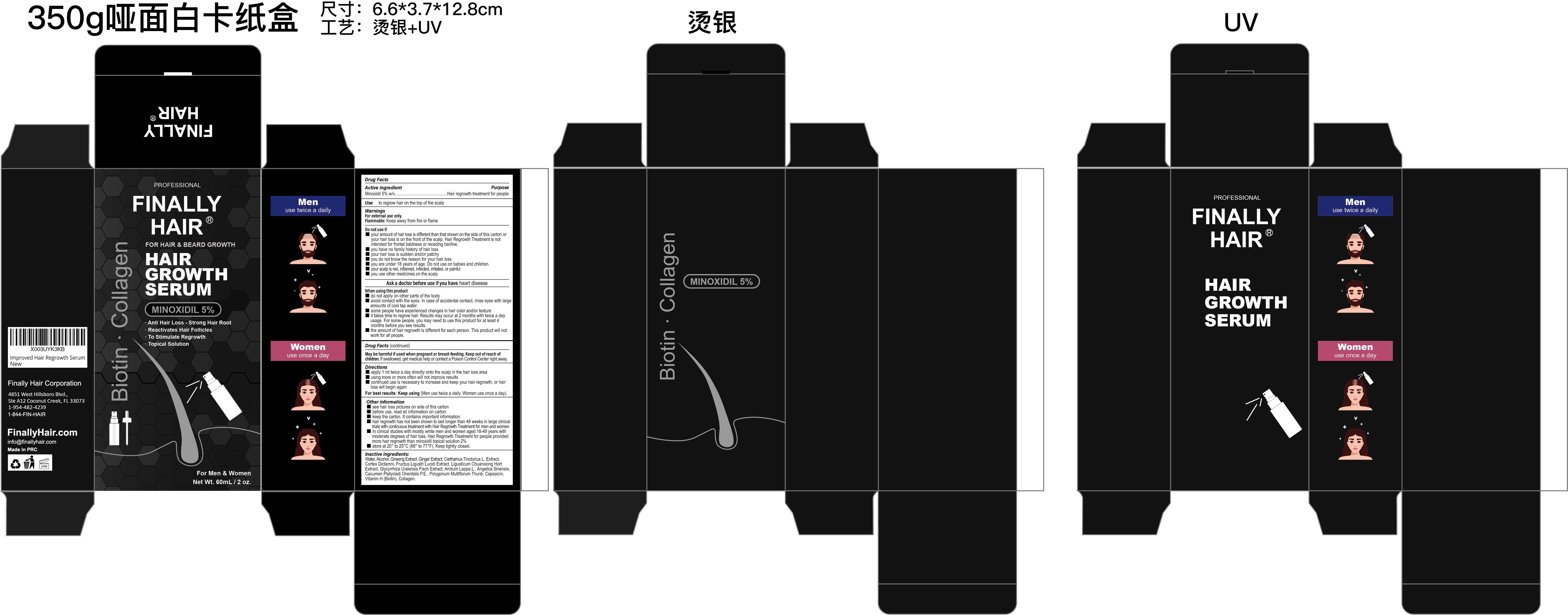 DRUG LABEL: FINALLY HAIR MINOXIDIL 5% HAIR GROWTH SERUM
NDC: 81653-012 | Form: LIQUID
Manufacturer: Guangzhou Jianyuan Biological Technology Co.,Ltd
Category: otc | Type: HUMAN OTC DRUG LABEL
Date: 20231219

ACTIVE INGREDIENTS: MINOXIDIL 5 g/100 mL
INACTIVE INGREDIENTS: ANGELICA SINENSIS ROOT; BOK-CHOY; ARCTIUM LAPPA WHOLE; REYNOUTRIA MULTIFLORA ROOT OIL; CARTHAMUS TINCTORIUS WHOLE; RUBUS CHINGII WHOLE; ASIAN GINSENG; GINGER; DICTAMNUS DASYCARPUS ROOT; CAPSAICIN; COLLAGEN ALPHA-1(II) CHAIN; BIOTIN; LIGUSTICUM SINENSE SUBSP. CHUANXIONG ROOT; GLYCYRRHIZA URALENSIS WHOLE; WATER; ALCOHOL

Active Ingredient

Minoxidil 5% w/ v.

Purpose

Hair regrowth treatment for people

Use

to regrow hair on the top of the scalp

Warnings

For external use only.
Flammable: Keep away from fire or flame

Do not use

■your amount of hair loss is different than that shown on the side of this carton or your hair loss is on the front of the scalp. Hair Regrowth Treatment is not intended for frontal baldness or receding hairline.
■ you have no family history of hair loss
■ your hair loss is sudden and/or patchy
■ you do not know the reason for your hair loss
■ you are under 18 years of age. Do not use on babies and children.
■ your scalp is red, inflamed, infected, irritated, or painful
■ you use other medicines on the scalp

When Using

■ do not apply on other parts of the body
■ avoid contact with the eyes. In case of accidental contact, rinse eyes with large amounts of cool tap water.
■ some people have experienced changes in hair color and/or texture
■ it takes time to regrow hair. Results may occur at 2 months with twice a day usage. For some people, you may need to use this product for at least 4 months before you see results.
■ the amount of hair regrowth is different for each person. This product will not work for all people.

Stop Use

.Chest pain, rapid heartbeat, faintness, or dizziness occurs.
.Sudden, unexplained weight gain occurs.
.Your hands or feet swell.
. Scalp irritation or redness occurs.
.Unwanted facial hair growth occurs.
·You do not see hair regrowth in 4 months.

Ask Doctor

If have heart disease.

Keep Oot Of Reach Of Children

Yes, Keep Oot Of Reach Of Children

Directions

■ apply 1 ml twice a day directly onto the scalp in the hair loss area
■ using more or more often will not improve results
■ continued use is necessary to increase and keep your hair regrowth, or hair loss will begin again
For best results: Keep using (Men use twice a daily. Women use once a day).

Other information

■ see hair loss pictures on side of this carton
■ before use, read all information on carton
■ keep the carton. It contains important information.
■ hair regrowth has not been shown to last longer than 48 weeks in large clinical
trials with continuous treatment with Hair Regrowth Treatment for men and women
■ In clinical studies with mostly white men and women aged 18-49 years with
moderate degrees of hair loss, Hair Regrowth Treatment for people provided
more hair regrowth than minoxidil topical solution 2%
■ store at 20° to 25°C (68° to 77°F). Keep tightly closed.

Inactive ingredients

Water, Alcohol, Ginseng Extract, Ginger Extract, Carthamus Tinctorius L. Extract,
Cortex Dictamni, Fructus Ligustri Lucidi Extract, Ligusticum Chuanxiong Hort
Extract, Glycyrrhiza Uralensis Fisch Extract, Arctium Lappa L., Angelica Sinensis,
Cacumen Platycladi Orientalis P.E., Polygonum Multiflorum Thunb, Capsaicin,
Vitamin H (Biotin), Collagen.

Questions

Info@finallyhair.com